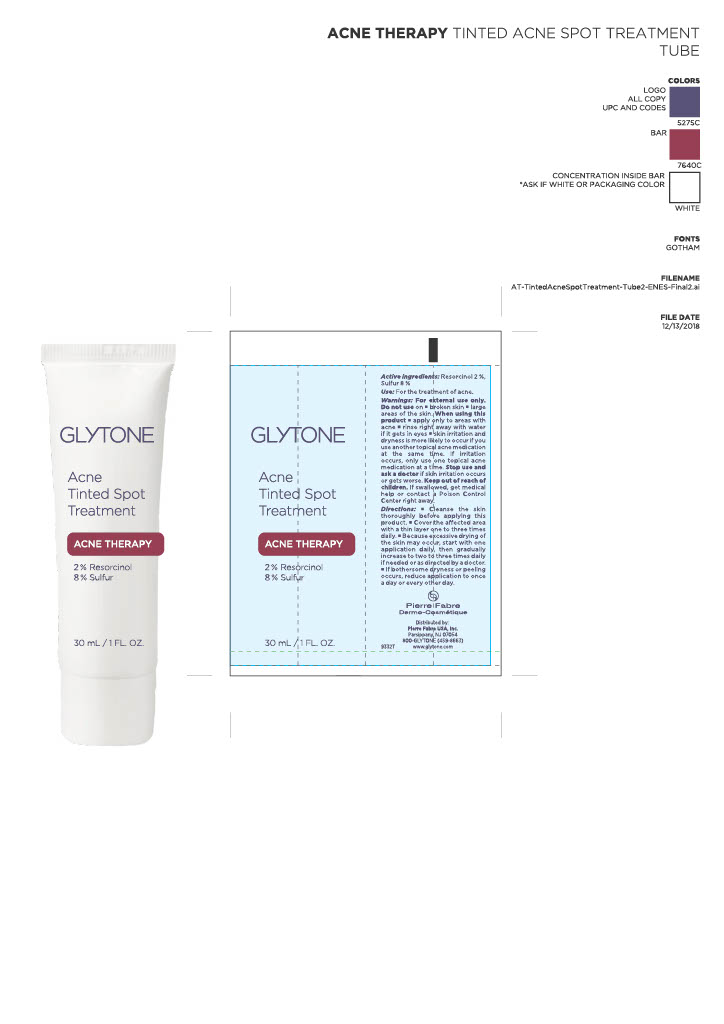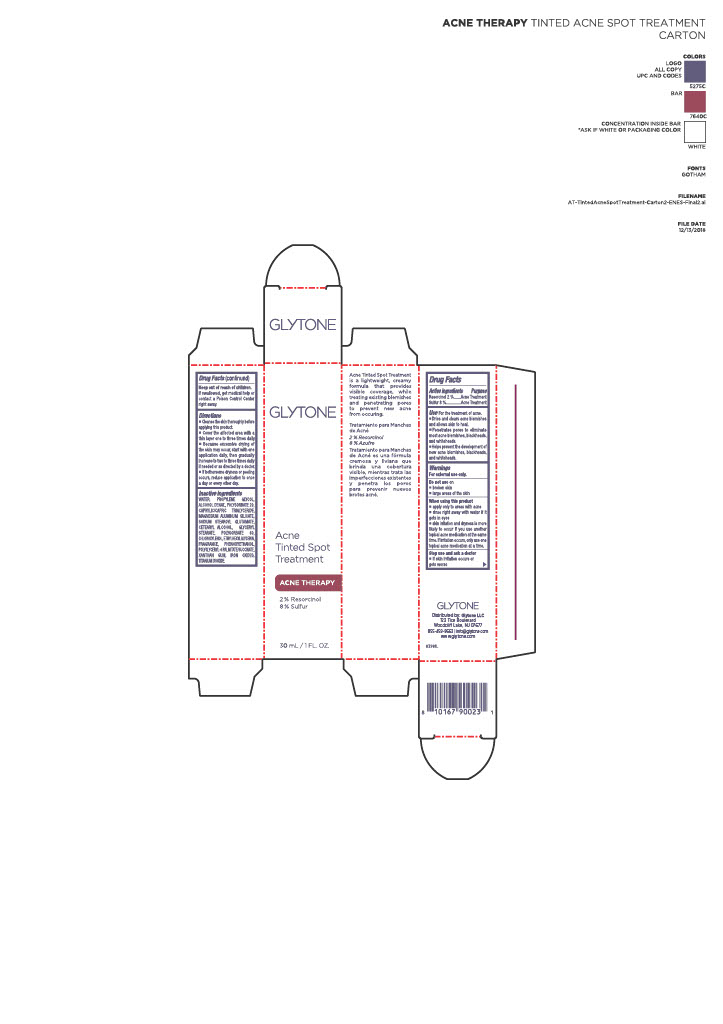 DRUG LABEL: Acne Tinted Spot Treatment
NDC: 84262-028 | Form: CREAM
Manufacturer: Glytone, LLC
Category: otc | Type: HUMAN OTC DRUG LABEL
Date: 20250625

ACTIVE INGREDIENTS: 4,6-BIS(1-METHYLPENTYL)RESORCINOL 2 g/100 g; SULFUR 8 g/100 g
INACTIVE INGREDIENTS: WATER; PROPYLENE GLYCOL; POLYSORBATE 20; CAPRYLIC/CAPRIC TRIGLYCERIDE; MAGNESIUM ALUMINUM SILICATE; SODIUM STEAROYL GLUTAMATE; CETEARYL ALCOHOL; GLYCERYL STEARATE; POLYSORBATE 60; CHLOROXYLENOL; ETHYLHEXYLGLYCERIN; FRAGRANCE 13576; PHENOXYETHANOL; XANTHAN GUM; BROWN IRON OXIDE; TITANIUM DIOXIDE; ALCOHOL; SAFFLOWER SEED OIL POLYGLYCERYL-6 ESTERS

INDICATIONS AND USAGE

For the treatment of acne.
Dries and helps clear up acne pimples and blackheads.
Helps prevent new acne blemishes from forming

WARNINGS AND PRECAUTIONS

For external use only

Do not use
• on broken skin
• on large areas of the body

When using this product
• avoid contact with eyes. If contact occurs, rinse thoroughly with water
• apply only to areas with acne
• skin irritation and dryness are more likely to occur if you use another topical acne medication at the same time. If irritation occurs, use only one topical acne medication at a time

Stop use and ask a doctor if
• skin irritation becomes severe

Keep out of reach of children. If swallowed, get medical help or contact a Poison Control Center right away.

DOSAGE AND ADMINISTRATION

Clean the skin thoroughly before applying this product
Cover the entire affected area with a thin layer 1 to 3 times daily
Because excessive drying of the skin may occur, start with 1 application daily, then gradually increase to 2 or 3 times daily if needed or as directed by a doctor
If bothersome dryness or peeling occurs, reduce application to once a day or every other day

INACTIVE INGREDIENT

Water, Cyclopentasiloxane, Isocetyl Stearate, Polysorbate 60, Sorbitan Stearate, Steareth-2, PEG-100 Stearate, Steareth-21, Glycerin, Glyceryl Stearate, Butylene Glycol, Cetearyl Alcohol, Bentonite, Dimethicone Crosspolymer, Diazolidinyl Urea, Sodium Hydroxide, Methylparaben, Propylparaben, Fragrance (Parfum), Iron Oxides (CI 77491, CI 77492, CI 77499), Titanium Dioxide (CI 77891)

ACTIVE INGREDIENT

Sulfur 8% – Acne treatment
Resorcinol 2% – Acne treatment

Keep out of reach of children.
If swallowed, get medical help or contact a Poison Control Center right away.

OTHER SAFETY INFORMATION

• Store at room temperature
• Avoid excessive heat and direct sunlight

DOSAGE AND ADMINISTRATION

• Clean the skin thoroughly before applying this product
• Cover the entire affected area with a thin layer 1 to 3 times daily
• Because excessive drying may occur, start with 1 application daily, then gradually increase to 2 or 3 times daily if needed
• If bothersome dryness or peeling occurs, reduce application to once a day or every other day

RECENT MAJOR CHANGES

Updated section type

Keep out of reach of children.
If swallowed, get medical help or contact a Poison Control Center right away.

Purpose
Acne treatment